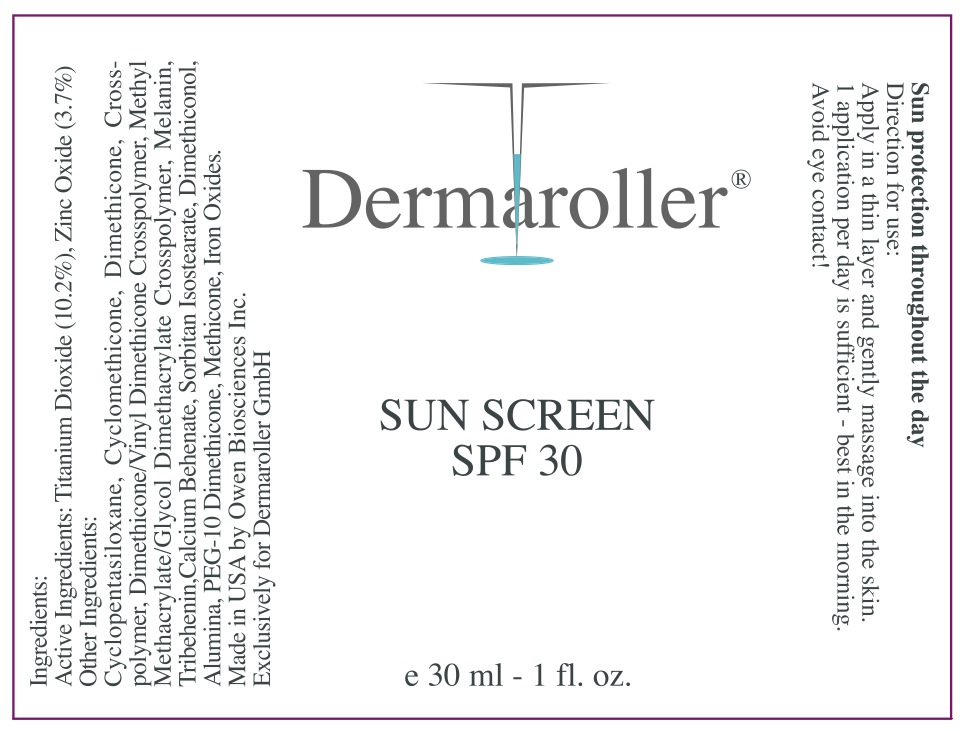 DRUG LABEL: Anhydrous SPF 30
NDC: 59958-200 | Form: CREAM
Manufacturer: Owen Biosciences, Inc.
Category: otc | Type: HUMAN OTC DRUG LABEL
Date: 20260108

ACTIVE INGREDIENTS: TITANIUM DIOXIDE 10.2 g/100 g; ZINC OXIDE 3.7 g/100 g
INACTIVE INGREDIENTS: CYCLOMETHICONE 17.5 g/100 g; TRIBEHENIN 1 g/100 g; FERRIC OXIDE RED 0.09 g/100 g; FERRIC OXIDE YELLOW 0.25 g/100 g; FERROSOFERRIC OXIDE

Owen Biosciences Anhydrous SPF 30 30ml

Drug Facts

Active ingredients Purpose

Titanium Dioxide 10.20% Sunscreen

Zinc Oxide 3.70% Sunscreen

USES

Helps Prevent sunburn.

Higher SPF gives more sunburn protection

Provides moderate protection against sunburn.

Warnings

For external use only. When using this product

keep out of eyes. Rinse with water to remove.

Stop use and ask doctor if rash and irritation

develops and lasts. Keep out of reach of

children. If swallowed, get medical help or

contact poison control center right away.

Keep out of reach of children

Keep out of reach of

children.

Directions

Apply evenly before sun exposure and as

needed. For children under 6 months of age: ask

a doctor. Reapply as needed or after towel

drying, swimming or perspiring.

Directions

Apply evenly before sun exposure and as

needed. For children under 6 months of age: ask

a doctor. Reapply as needed or after towel

drying, swimming or perspiring.

Other Information

Sun alert: Limiting sun exposure, wearing protective clothing, and using sunscreens may reduce the risk of skin cancer, and other

harmful effects of the sun.

Inactive Ingredients

Cyclopentasiloxane, Cyclomethicone, Dimethicone Crosspolymer, Methyl Methacrylate/Glycol Dimethacrylate Crosspolymer,

Dimethicone/Vinyl Dimethicone Crosspolymer, Melanin, Tribehenin, Calcium Behenate, Sorbitan Isostearate, Dimethiconol,

Alumina, PEG-10 Dimethicone, Methicone, Iron Oxides.